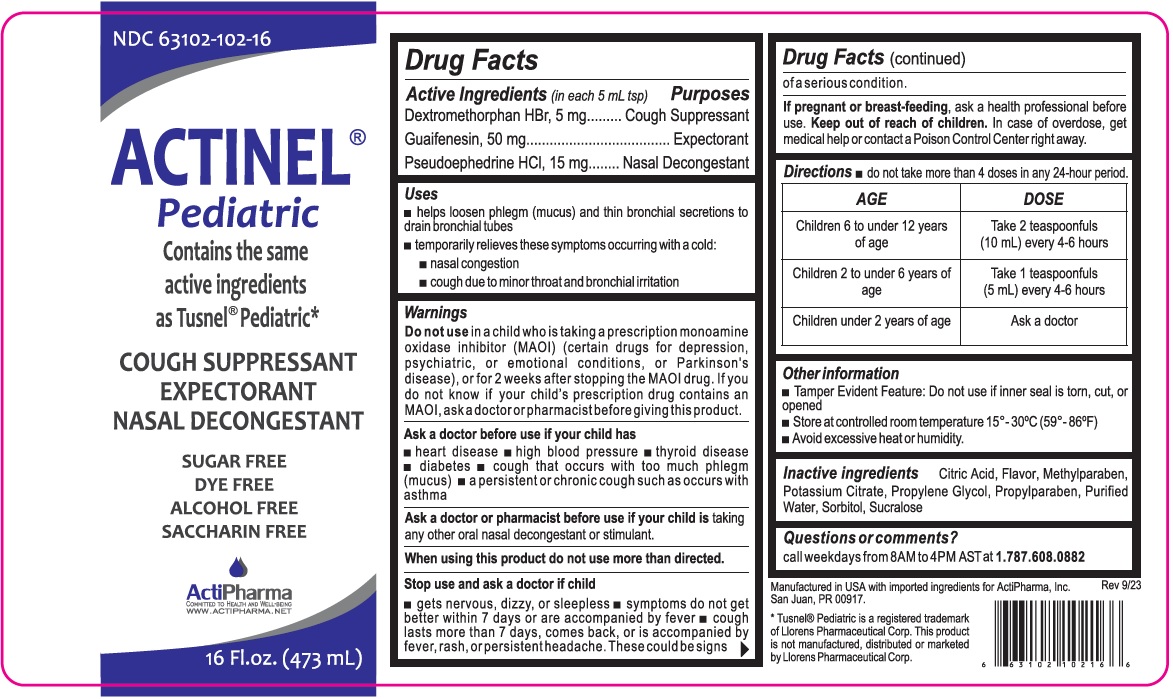 DRUG LABEL: ACTINEL PEDIATRIC
NDC: 63102-102 | Form: SOLUTION
Manufacturer: ACTIPHARMA, LLC
Category: otc | Type: HUMAN OTC DRUG LABEL
Date: 20250708

ACTIVE INGREDIENTS: DEXTROMETHORPHAN HYDROBROMIDE 5 mg/5 mL; GUAIFENESIN 50 mg/5 mL; PSEUDOEPHEDRINE HYDROCHLORIDE 15 mg/5 mL
INACTIVE INGREDIENTS: CITRIC ACID MONOHYDRATE; METHYLPARABEN; POTASSIUM CITRATE; PROPYLENE GLYCOL; PROPYLPARABEN; WATER; SORBITOL; SUCRALOSE

ACTINEL® Pediatric

Active Ingredients (in each 5 mL tsp)

Dextromethorphan HBr, 5 mg
Guaifenesin, 50 mg
Pseudoephedrine HCl, 15 mg

Purposes

Cough Suppressant
Expectorant
Nasal Decongestant

Uses

• helps loosen phlegm (mucus) and thin bronchial secretions to drain bronchial tubes
• temporarily relieves these symptoms occurring with a cold:
• nasal congestion
• cough due to minor throat and bronchial irritation

Warnings

Do not use in a child who is taking a prescription monoamine oxidase inhibitor (MAOI) (certain drugs for depression, psychiatric, or emotional conditions, or Parkinson’s disease), or for 2 weeks after stopping the MAOI drug. If you do not know if your child's prescription drug contains an MAOI, ask a doctor or pharmacist before giving this product.

Ask a doctor before use if your child has
• heart disease • high blood pressure • thyroid disease • diabetes • cough that occurs with too much phlegm (mucus) • a persistent or chronic cough such as occurs with asthma

Ask a doctor or pharmacist before use if your child is taking any other oral nasal decongestant or stimulant.

When using this product do not use more than directed.

Stop use and ask a doctor if child
• gets nervous, dizzy, or sleepless • symptoms do not get better within 7 days or are accompanied by fever • cough lasts more than 7 days, comes back, or is accompanied by fever, rash, or persistent headache. These could be signs of a serious condition.

If pregnant or breast-feeding, ask a health professional before use.

Keep out of reach of children. In case of overdose, get medical help or contact a Poison Control Center right away.

Directions

• do not take more than 4 doses in any 24-hour period.

AGE | DOSE
Children 6 to under 12 years of age | Take 2 teaspoonfuls (10 mL) every 4-6 hours
Children 2 to under 6 years of age | Take 1 teaspoonfuls (5 mL) every 4-6 hours
Children under 2 years of age | Ask a doctor

Other information

• Tamper Evident Feature: Do not use if inner seal is torn, cut, or opened
• Store at controlled room temperature 15°- 30°C (59° -86°F)
• Avoid excessive heat or humidity.

Inactive ingredients

Citric Acid, Flavor, Methylparaben, Potassium Citrate, Propylene Glycol, Propylparaben, Purified Water, Sorbitol, Sucralose

Questions or comments?

call weekdays from 8AM to 4PM AST at 1.787.608.0882

Contains the same active ingredients as Tusnel® Pediatric*

SUGAR FREE
DYE FREE
ALCOHOL FREE
SACCHARIN FREE

COMMITTED TO HEALTH AND WELL-BEING
WWW.ACTIPHARMA.NET

Manufactured in USA with imported ingredients for ActiPharma, Inc.
San Juan, PR 00917.

* Tusnel® Pediatric is a registered trademark of Llorens Pharmaceutical Corp. This product is not manufactured, distributed or marketed by Llorens Pharmaceutical Corp.